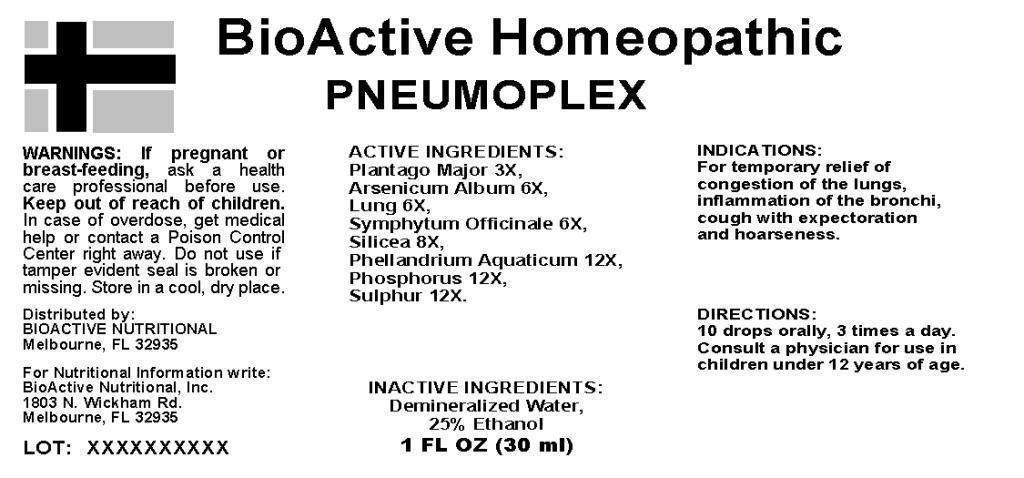 DRUG LABEL: PNEUMOPLEX
NDC: 43857-0190 | Form: LIQUID
Manufacturer: BioActive Nutritional, Inc.
Category: homeopathic | Type: HUMAN OTC DRUG LABEL
Date: 20240326

ACTIVE INGREDIENTS: PLANTAGO MAJOR WHOLE 3 [hp_X]/1 mL; ARSENIC TRIOXIDE 6 [hp_X]/1 mL; BEEF LUNG 6 [hp_X]/1 mL; COMFREY ROOT 6 [hp_X]/1 mL; SILICON DIOXIDE 8 [hp_X]/1 mL; OENANTHE AQUATICA FRUIT 12 [hp_X]/1 mL; PHOSPHORUS 12 [hp_X]/1 mL; SULFUR 12 [hp_X]/1 mL
INACTIVE INGREDIENTS: WATER; ALCOHOL

DRUG FACTS:

ACTIVE INGREDIENTS:

Plantago Major 3X, Arsenicum Album 6X, Lung (Bovine) 6X, Symphytum Officinale 6X, Silicea 8X, Phellandrium Aquaticum 12X, Phosphorus 12X, Sulphur 12X.

INDICATIONS:

For temporary relief of congestion of the lungs, inflammation of the bronchi, cough with expectoration and hoarseness.

WARNINGS:

If pregnant or breast-feeding, ask a health care professional before use.

Keep out of reach of children. In case of overdose, get medical help or contact a Poison Control Center right away.

Do not use if tamper evident seal is broken or missing.

STORAGE:

Store in a cool, dry place.

DIRECTIONS:

10 drops orally, 3 times a day. Consult a physician for use in children under 12 years of age.

INACTIVE INGREDIENTS:

Demineralized Water, 25% Ethanol

KEEP OUT OF REACH OF CHILDREN:

In case of overdose, get medical help or contact a Poison Control Center right away.

INDICATIONS:

For temporary relief of congestion of the lungs, inflammation of the bronchi, cough with expectoration and hoarseness.

QUESTIONS:

Distributed by:

BIOACTIVE NUTRITIONAL

Melbourne, FL 32935

For Nutritional Information write:

BioActive Nutritional, Inc.

1803 N. Wickham Rd.

Melbourne, FL 32935

PACKAGE DISPLAY LABEL:

BioActive Homeopatchic

PNEUMOPLEX

1 FL OZ (30 mL)